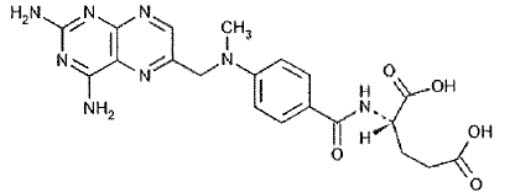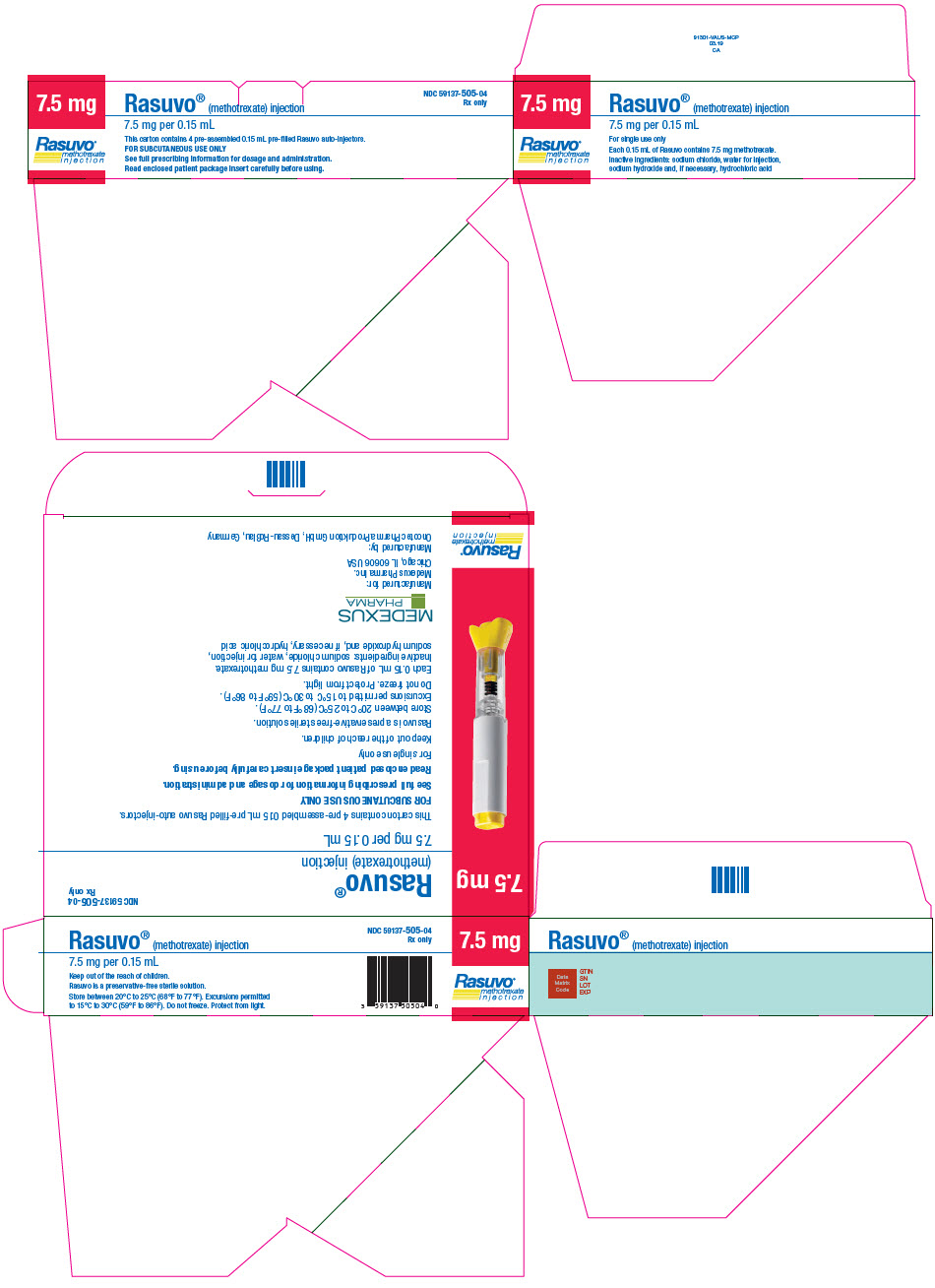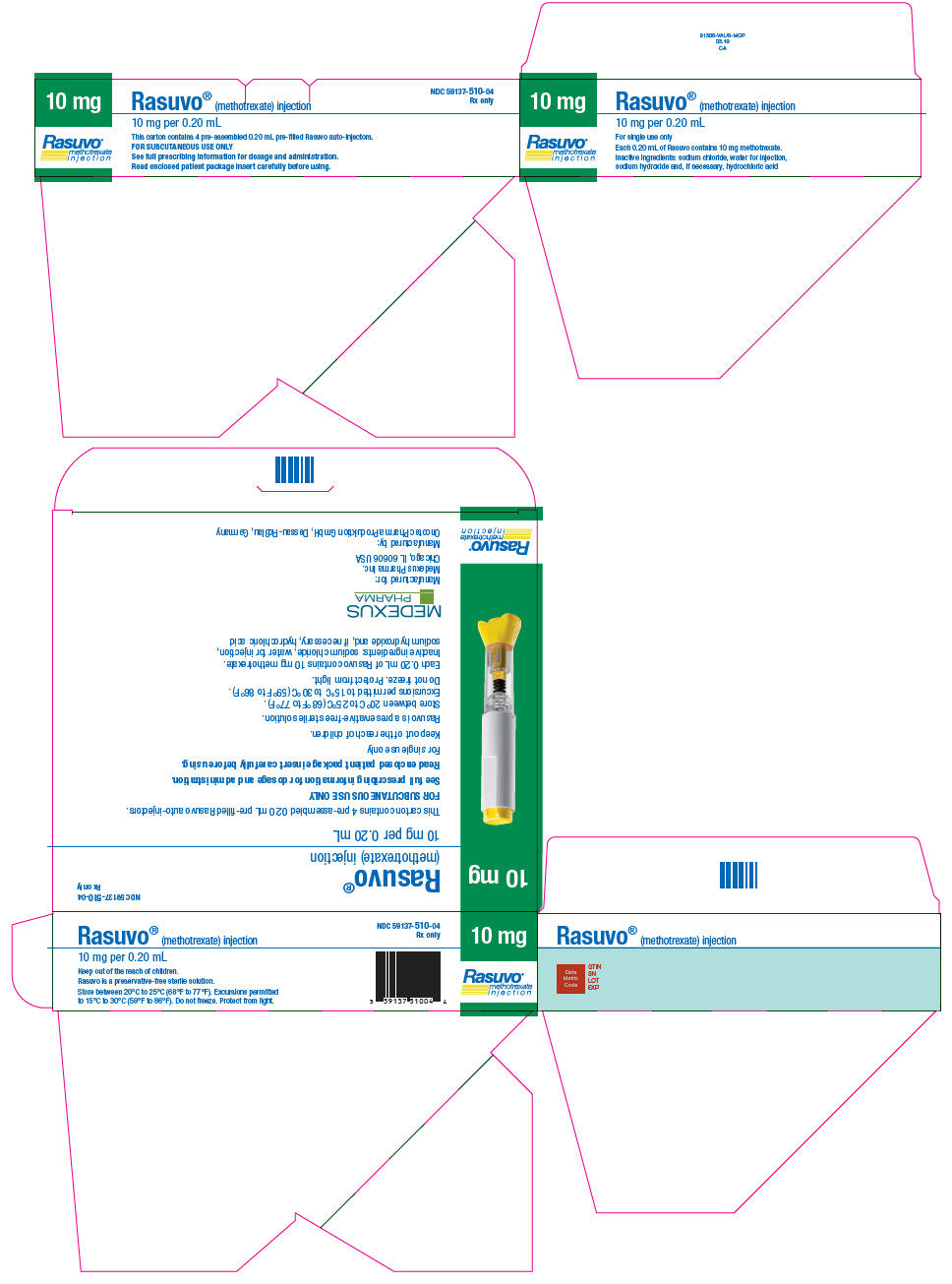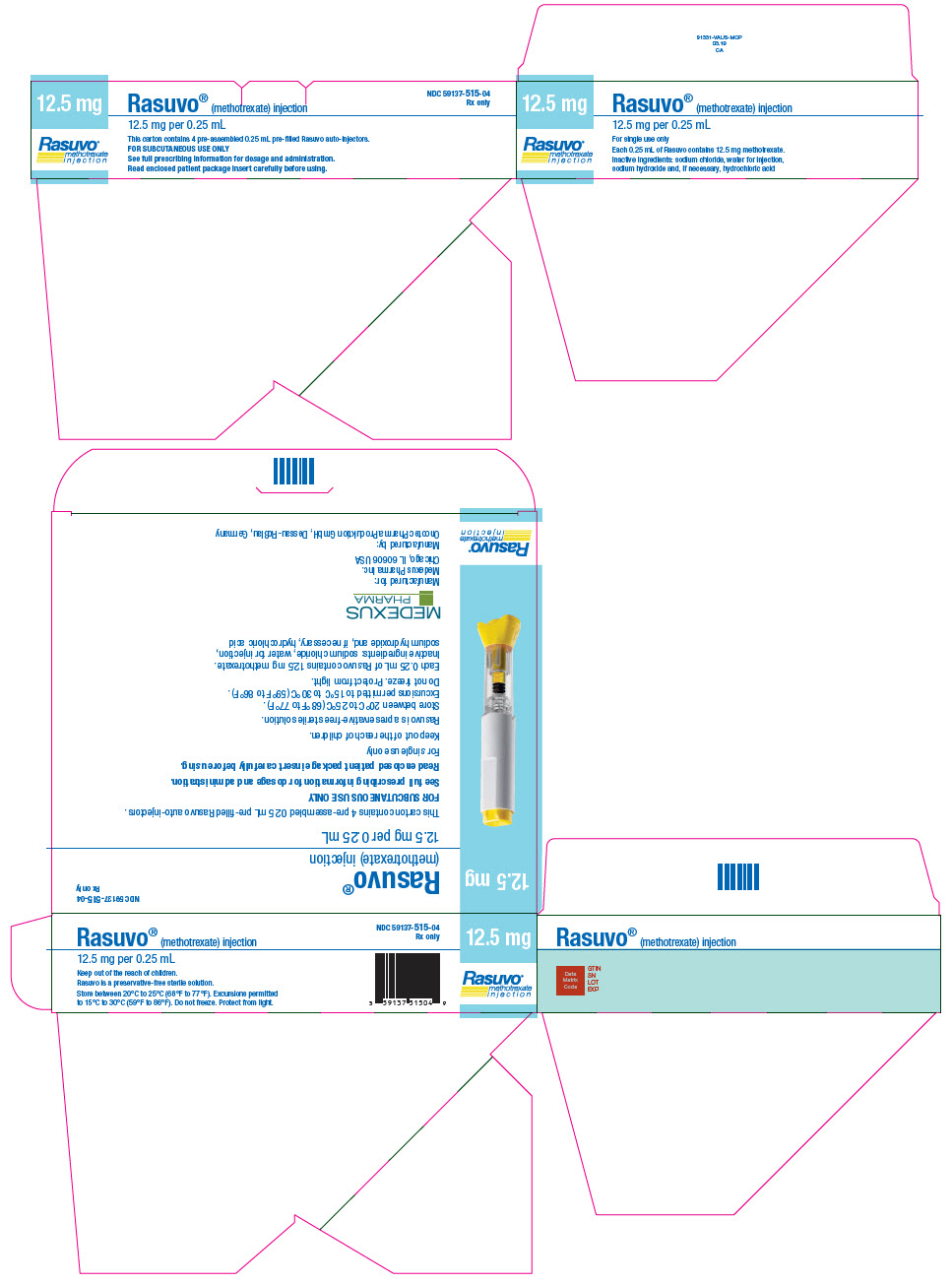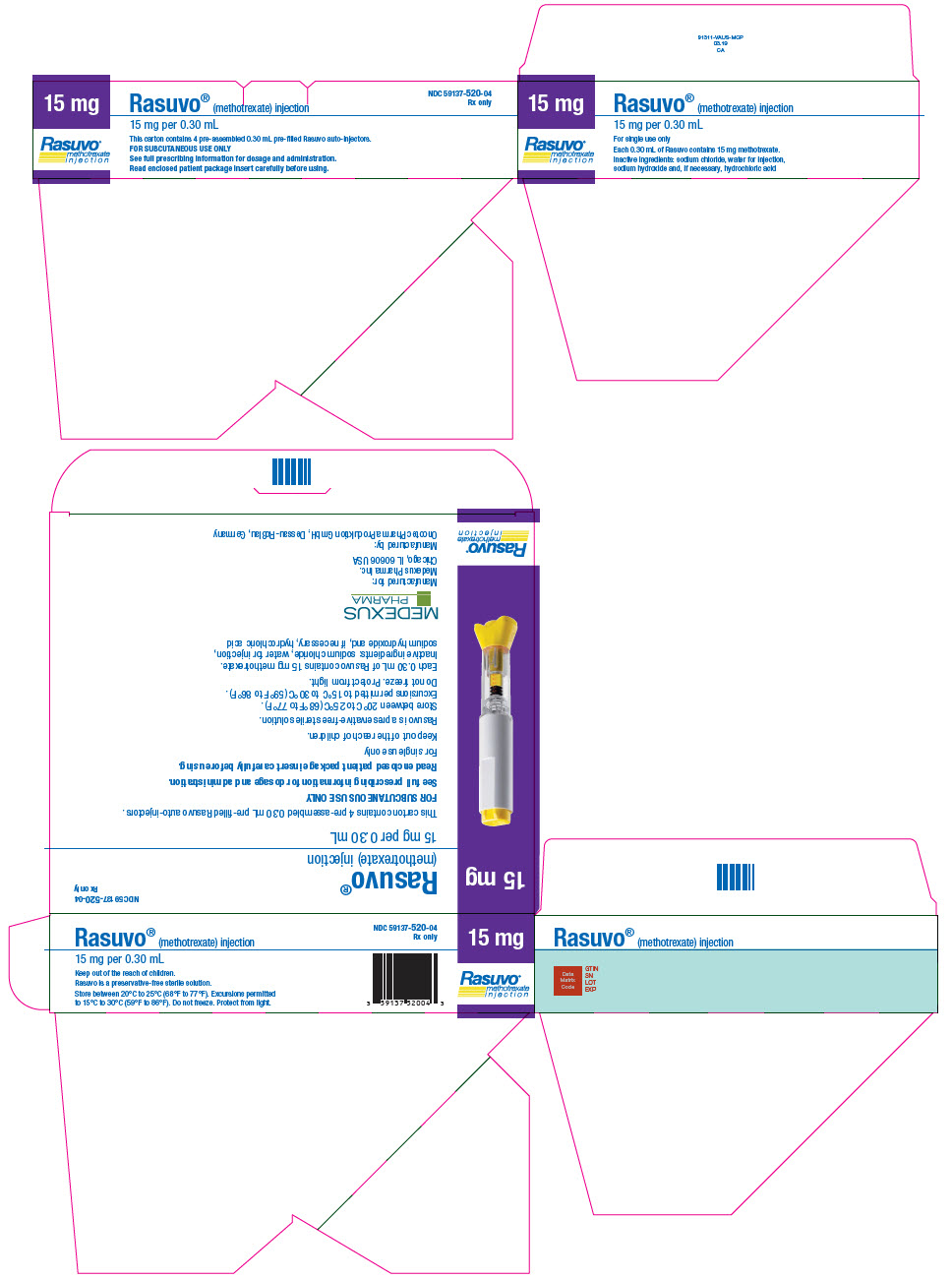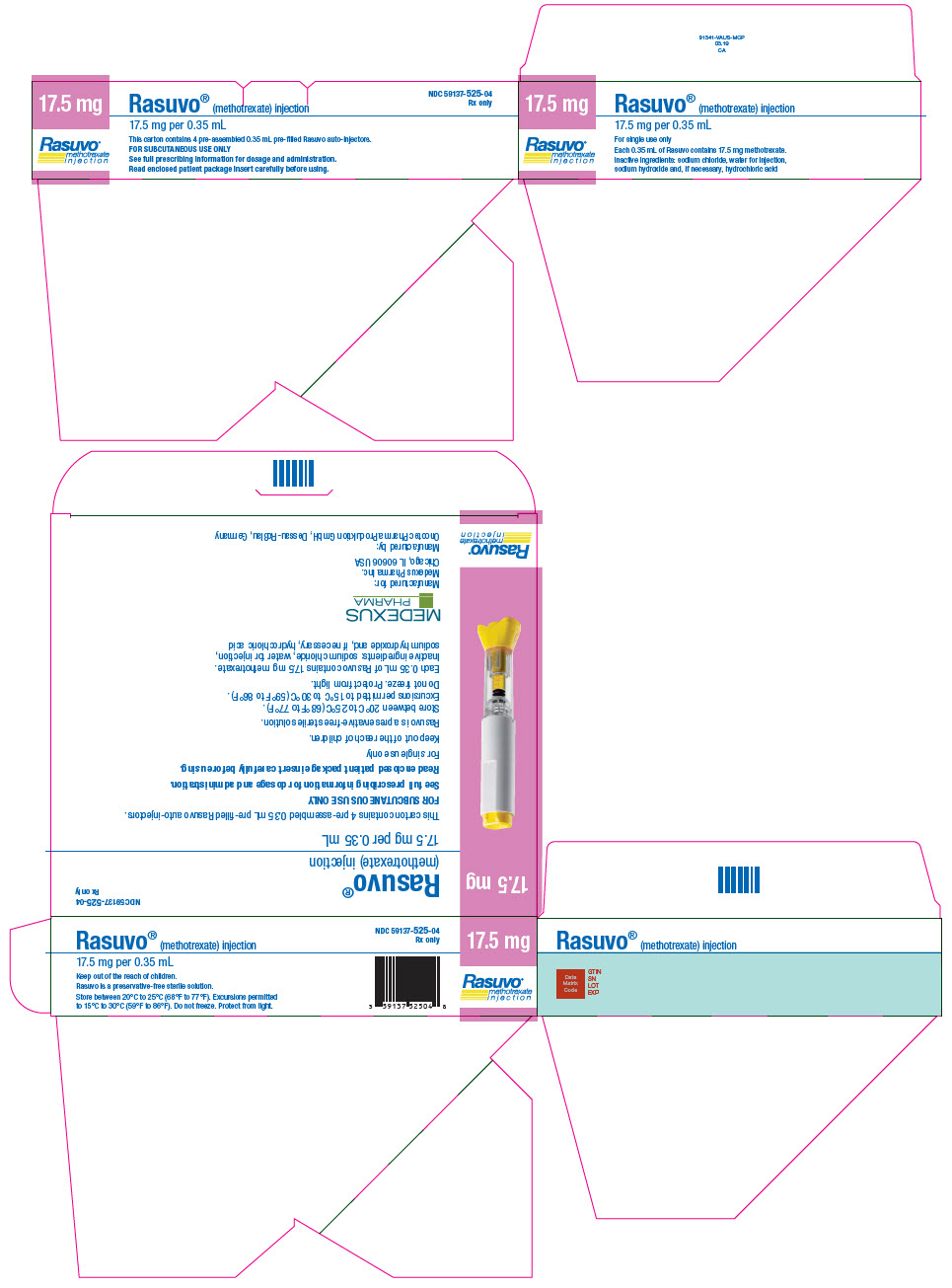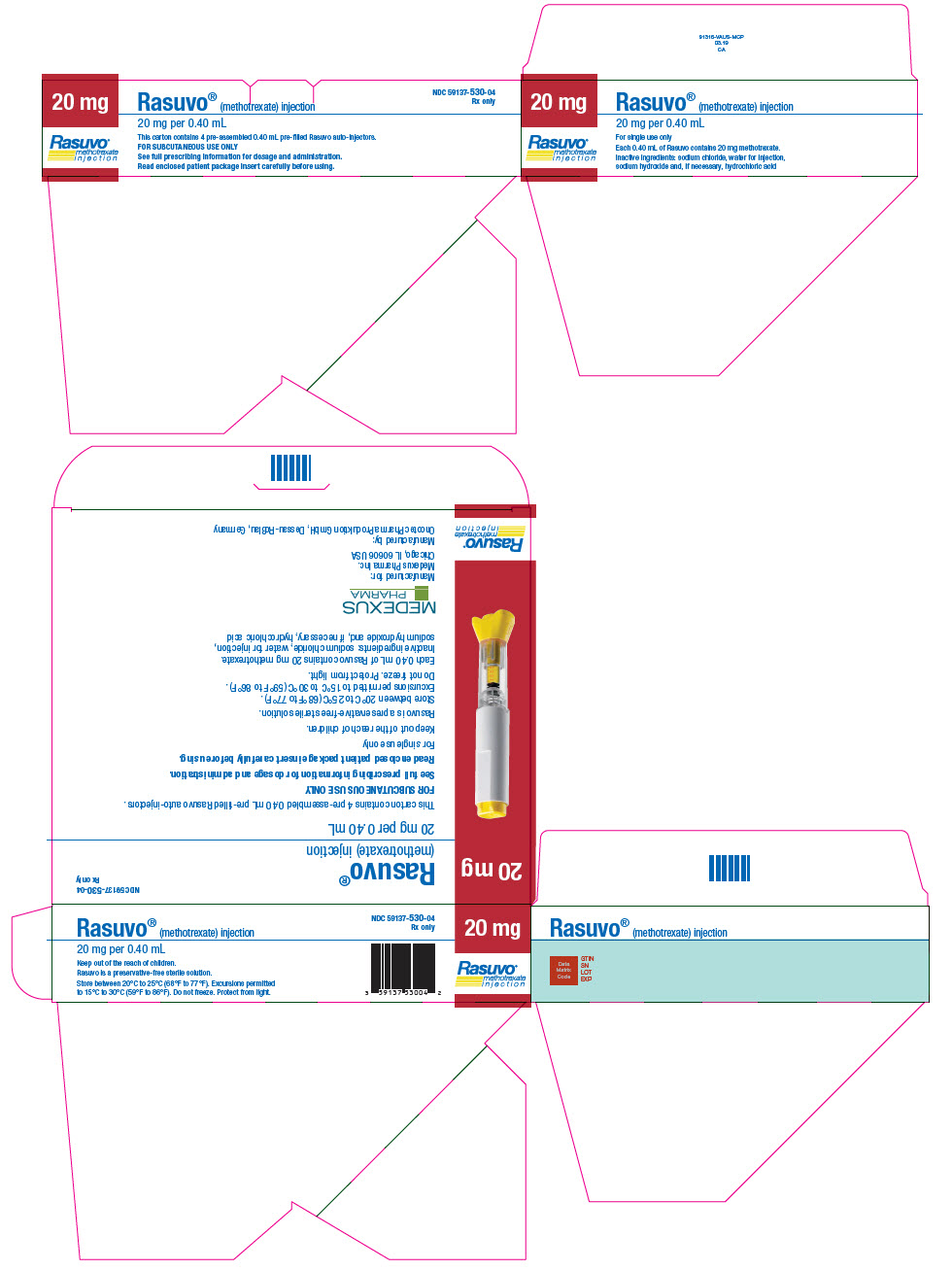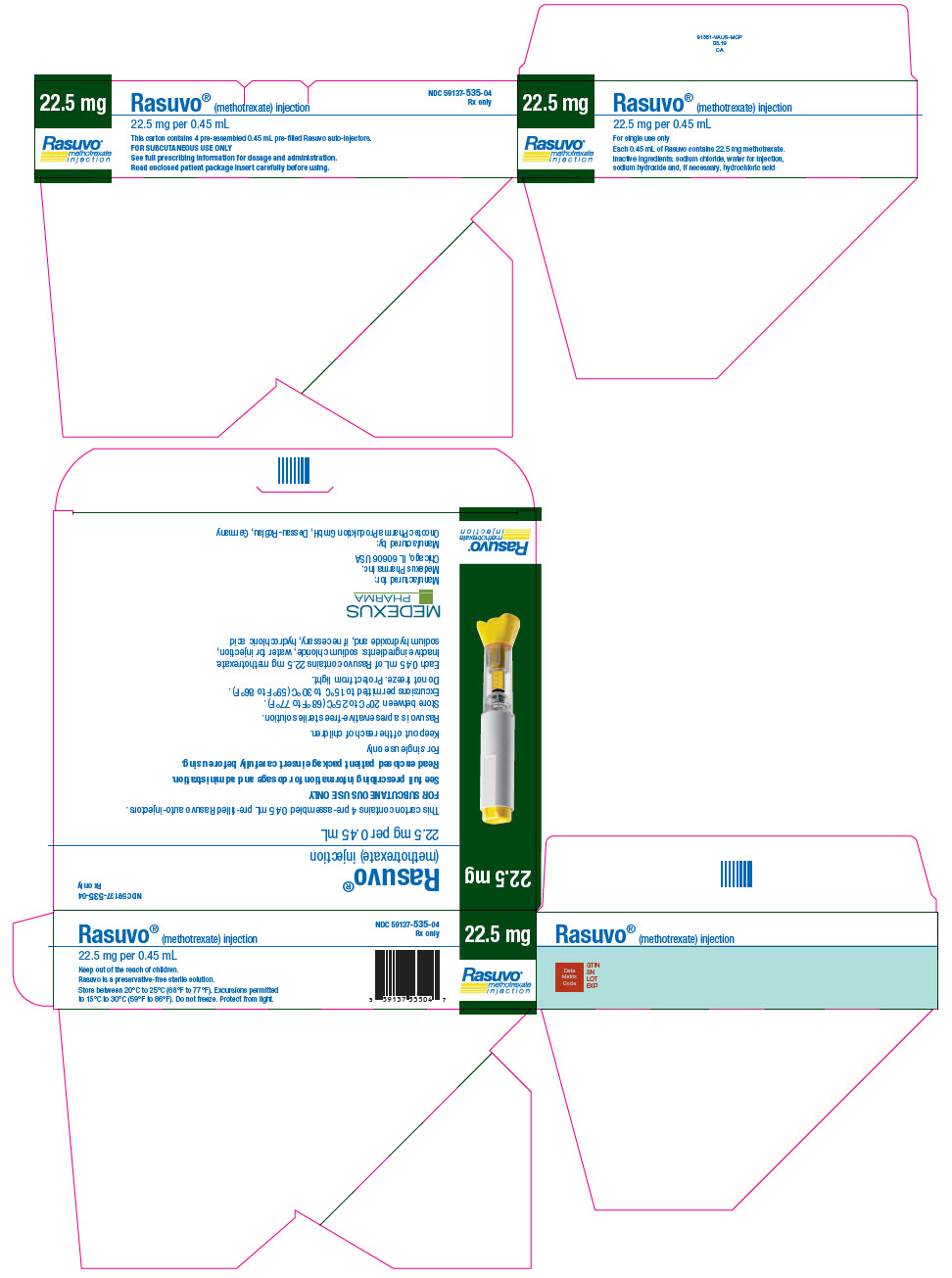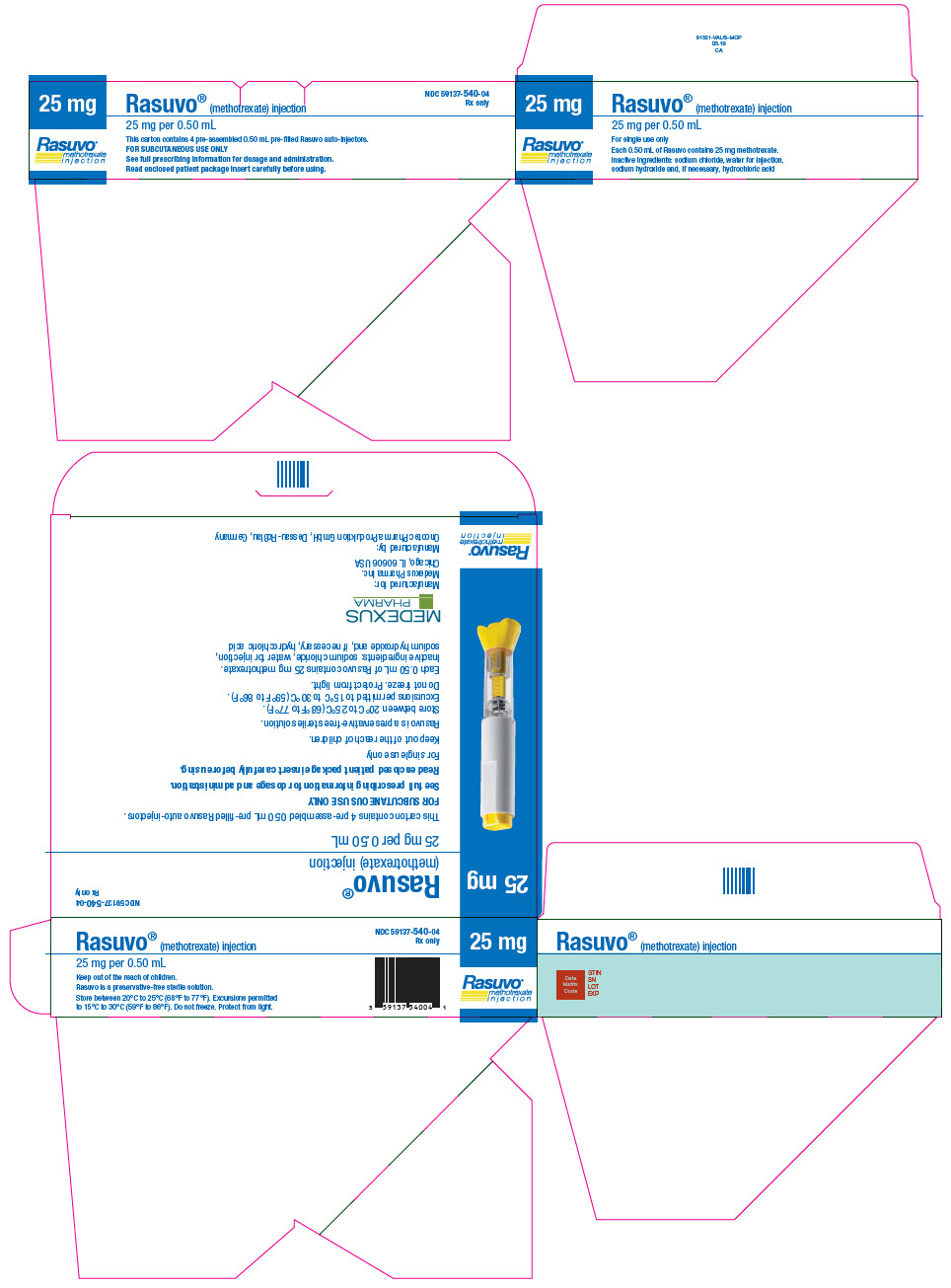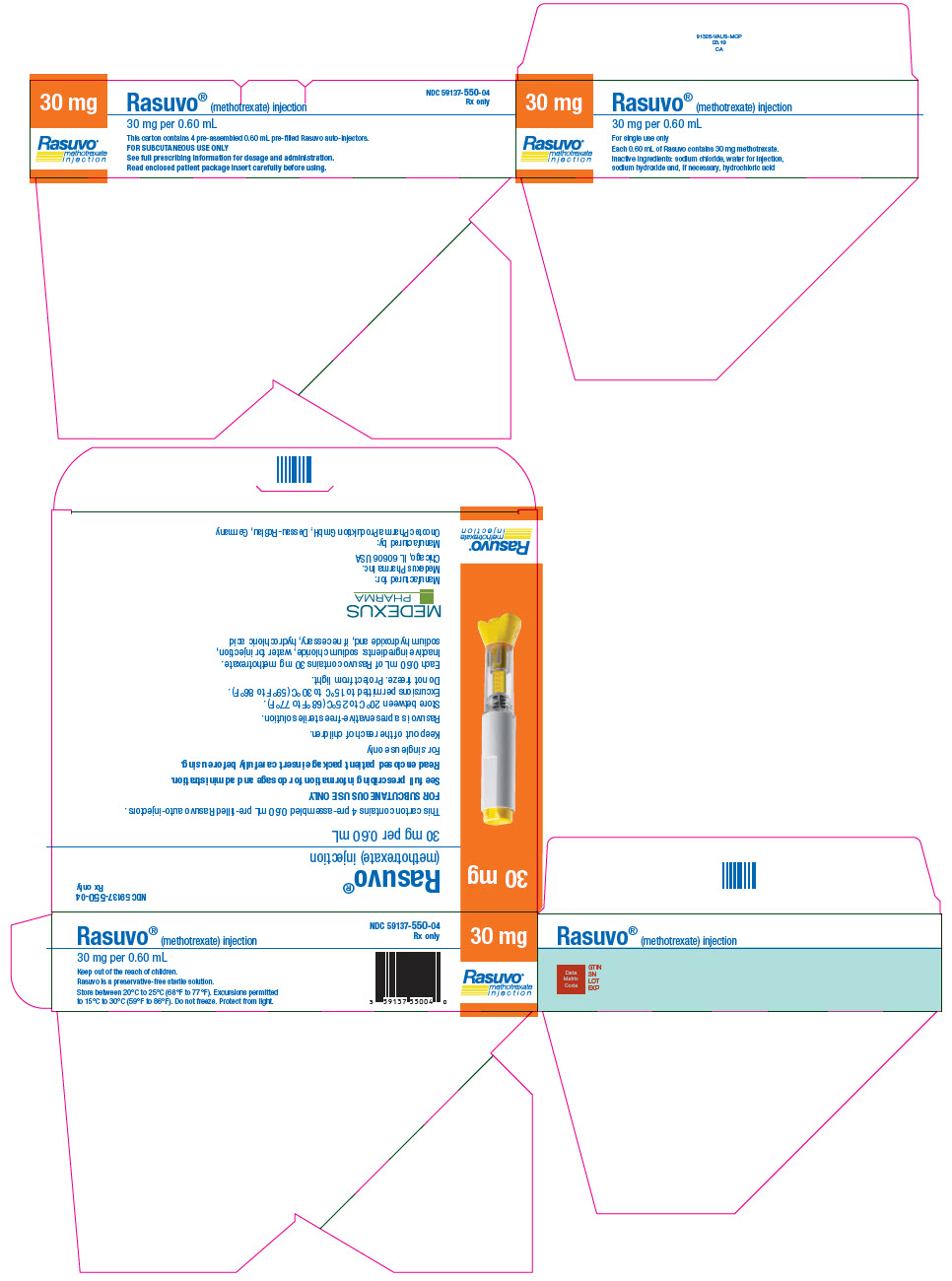 DRUG LABEL: Rasuvo
NDC: 59137-505 | Form: INJECTION, SOLUTION
Manufacturer: Medexus Pharma Inc.
Category: prescription | Type: HUMAN PRESCRIPTION DRUG LABEL
Date: 20251215

ACTIVE INGREDIENTS: methotrexate sodium 7.5 mg/0.15 mL
INACTIVE INGREDIENTS: sodium chloride; water; sodium hydroxide; hydrochloric acid

HIGHLIGHTS OF PRESCRIBING INFORMATION

These highlights do not include all the information needed to use RASUVO® safely and effectively. See full prescribing information for RASUVO.
RASUVO (methotrexate) injection, for subcutaneous use
Initial U.S. Approval: 1953

WARNING: SEVERE TOXIC REACTIONS, INCLUDING EMBRYO-FETAL TOXICITY AND DEATH

See full prescribing information for complete boxed warning.

- Serious toxic reactions and death have been reported with the use of methotrexate. Patients should be closely monitored for bone marrow, liver, lung, skin, and kidney toxicities (5.1).
- Methotrexate can cause embryo-fetal toxicity, including fetal death. Use is contraindicated during pregnancy (4). Advise females and males of reproductive potential to use effective contraception during and after treatment with methotrexate. (5.2, 8.1, 8.3).
- Unexpectedly severe (sometimes fatal) bone marrow suppression, aplastic anemia, and gastrointestinal toxicity have been reported with concomitant administration of methotrexate (usually in high dosage) along with some nonsteroidal anti-inflammatory drugs (NSAIDs) (5.1).
- Hepatotoxicity, fibrosis, and cirrhosis may occur after prolonged use (5.1).
- Methotrexate may cause interstitial pneumonitis at any time during therapy and has been reported at low doses. Pulmonary symptoms (especially a dry, nonproductive cough) may require interruption of treatment and careful investigation (5.1).
- Diarrhea, ulcerative stomatitis, hemorrhagic enteritis, and death from intestinal perforation may occur (5.1).
- Severe, occasionally fatal, skin reactions have been reported (5.1).
- Potentially fatal opportunistic infections may occur (5.1).

1 INDICATIONS AND USAGE

Rasuvo is a folate analog metabolic inhibitor indicated for the:

- Management of patients with severe, active rheumatoid arthritis (RA) and polyarticular juvenile idiopathic arthritis (pJIA), who are intolerant of or had an inadequate response to first-line therapy (1.1)
- Symptomatic control of severe, recalcitrant, disabling psoriasis in adults who are not adequately responsive to other forms of therapy (1.2)

Limitation of Use

Rasuvo is not indicated for the treatment of neoplastic diseases (1.3).

2 DOSAGE AND ADMINISTRATION

- Rasuvo is for once weekly subcutaneous use only.
- Administer Rasuvo in the abdomen or thigh. (2.1)
- Use another formulation of methotrexate for patients requiring oral, intramuscular, intravenous, intra-arterial, or intrathecal dosing, doses less than 7.5 mg per week, doses above 30 mg per week, high-dose regimens, or dose adjustments of less than 2.5 mg increments (2.1)
- Starting doses of methotrexate:
  - RA: 7.5 mg once weekly of an oral or subcutaneous formulation (2.2)
  - pJIA: 10 mg/m2 once weekly (2.2)
  - Psoriasis: 10 to 25 mg once weekly of an oral, intramuscular, subcutaneous, or intravenous formulation (2.3)
- Adjust dose gradually to achieve an optimal response (2.2, 2.3)

3 DOSAGE FORMS AND STRENGTHS

Injection: Single-dose manually-triggered auto-injector delivering methotrexate in the following dosage strengths: 7.5 mg, 10 mg, 12.5 mg, 15 mg, 17.5 mg, 20 mg, 22.5 mg, 25 mg, 27.5 mg, and 30 mg (3).

4 CONTRAINDICATIONS

- Pregnancy (4)
- Alcoholism or liver disease (4)
- Immunodeficiency syndromes (4)
- Preexisting blood dyscrasias (4)
- Hypersensitivity to methotrexate (4)

5 WARNINGS AND PRECAUTIONS

- Organ system toxicity: Potential for serious toxicity. Only for use by physicians experienced in antimetabolite therapy (5.1).
- Effects on reproduction: May cause impairment of fertility, oligospermia and menstrual dysfunction (5.3)
- Laboratory tests: Monitor complete blood counts, renal function and liver function tests (5.4).
- Risks from improper dosing: Mistaken daily use has led to fatal toxicity (5.5)
- Patients with impaired renal function, ascites, or pleural effusions: Elimination is reduced (5.6).
- Dizziness and fatigue: May impair ability to drive or operate machinery (5.7)

6 ADVERSE REACTIONS

Common adverse reactions are: nausea, abdominal pain, dyspepsia, stomatitis/mouth sores, rash, nasopharyngitis, diarrhea, liver function test abnormalities, vomiting, headache, bronchitis, thrombocytopenia, alopecia, leukopenia, pancytopenia, dizziness, photosensitivity, and "burning of skin lesions" (6).

To report SUSPECTED ADVERSE REACTIONS, contact Medexus at 1-855-336-3322 or FDA at 1-800-FDA-1088 or www.fda.gov/medwatch.

7 DRUG INTERACTIONS

- Aspirin, NSAIDs, and steroids: concomitant use may elevate and prolong serum methotrexate levels and cause increased toxicity (7.1)
- Proton pump inhibitors: concomitant use may elevate and prolong serum methotrexate levels and cause increased toxicity (7.2)

8 USE IN SPECIFIC POPULATIONS

- Pediatric use: Safety and efficacy of methotrexate, including Rasuvo, have not been established in pediatric patients with psoriasis. Safety and efficacy of Rasuvo have not been established in pediatric patients with malignancy (8.4)
- Geriatric use: Use caution in dose selection (8.5)
- Lactation: Advise women not to breastfeed (8.2)

FULL PRESCRIBING INFORMATION

WARNING: SEVERE TOXIC REACTIONS, INCLUDING EMBRYO-FETAL TOXICITY AND DEATH

Rasuvo should be used only by physicians whose knowledge and experience include the use of antimetabolite therapy. Because of the possibility of serious toxic reactions (which can be fatal), Rasuvo should be used only in patients with psoriasis or rheumatoid arthritis with severe, recalcitrant, disabling disease which is not adequately responsive to other forms of therapy. Deaths have been reported with the use of methotrexate in the treatment of malignancy, psoriasis, and rheumatoid arthritis. Patients should be closely monitored for bone marrow, liver, lung, skin, and kidney toxicities. Patients should be informed by their physician of the risks involved and be under a physician's care throughout therapy [see Warnings and Precautions (5.1)].

1. Methotrexate can cause embryo-fetal toxicity, including fetal death. Use is contraindicated during pregnancy. Verify the pregnancy status of females of reproductive potential prior to initiating therapy. Advise females and males of reproductive potential to use effective contraception during and after treatment with Rasuvo [see Warnings and Precautions (5.2), Contraindications (4), and Use in Specific Populations (8.1, 8.3)].
2. Methotrexate elimination is reduced in patients with impaired renal functions, ascites, or pleural effusions. Such patients require especially careful monitoring for toxicity, and require dose reduction or, in some cases, discontinuation of Rasuvo administration [see Warnings and Precautions (5.6)].
3. Unexpectedly severe (sometimes fatal) bone marrow suppression, aplastic anemia, and gastrointestinal toxicity have been reported with concomitant administration of methotrexate (usually in high dosage) along with some nonsteroidal anti-inflammatory drugs (NSAIDs) [see Warnings and Precautions (5.1) and Drug Interactions(7.1)].
4. Methotrexate causes hepatotoxicity, fibrosis and cirrhosis, but generally only after prolonged use. Acutely, liver enzyme elevations are frequently seen. These are usually transient and asymptomatic, and also do not appear predictive of subsequent hepatic disease. Liver biopsy after sustained use often shows histologic changes, and fibrosis and cirrhosis have been reported; these latter lesions may not be preceded by symptoms or abnormal liver function tests in the psoriasis population. For this reason, periodic liver biopsies are usually recommended for psoriatic patients who are under long-term treatment. Persistent abnormalities in liver function tests may precede appearance of fibrosis or cirrhosis in the rheumatoid arthritis population [see Warnings and Precautions (5.1)].
5. Methotrexate-induced lung disease, including acute or chronic interstitial pneumonitis, is a potentially dangerous lesion, which may occur acutely at any time during therapy and has been reported at low doses. It is not always fully reversible and fatalities have been reported. Pulmonary symptoms (especially a dry, nonproductive cough) may require interruption of treatment and careful investigation [see Warnings and Precautions (5.1)].
6. Diarrhea and ulcerative stomatitis require interruption of therapy: otherwise, hemorrhagic enteritis and death from intestinal perforation may occur [see Warnings and Precautions (5.1)].
7. Malignant lymphomas, which may regress following withdrawal of methotrexate, may occur in patients receiving low-dose methotrexate and, thus, may not require cytotoxic treatment. Discontinue Rasuvo first and, if the lymphoma does not regress, appropriate treatment should be instituted [see Warnings and Precautions (5.8)].
8. Like other cytotoxic drugs, methotrexate may induce "tumor lysis syndrome" in patients with rapidly growing tumors [see Warnings and Precautions (5.9)].
9. Severe, occasionally fatal, skin reactions have been reported following single or multiple doses of methotrexate. Reactions have occurred within days of oral, intramuscular, intravenous, or intrathecal methotrexate administration. Recovery has been reported with discontinuation of therapy [see Warnings and Precautions (5.1)].
10. Potentially fatal opportunistic infections, especially Pneumocystis jiroveci pneumonia, may occur with methotrexate therapy [see Warnings and Precautions (5.1)].
11. Methotrexate given concomitantly with radiotherapy may increase the risk of soft tissue necrosis and osteonecrosis [see Warnings and Precautions (5.10)].

1 INDICATIONS AND USAGE

1.1 Rheumatoid Arthritis including Polyarticular Juvenile Idiopathic Arthritis

Rasuvo is indicated in the management of selected adults with severe, active rheumatoid arthritis (RA) (ACR criteria), or children with active polyarticular juvenile idiopathic arthritis (pJIA), who have had an insufficient therapeutic response to, or are intolerant of, an adequate trial of first-line therapy including full dose non-steroidal anti-inflammatory agents (NSAIDs).

1.2 Psoriasis

Rasuvo is indicated in adults for the symptomatic control of severe, recalcitrant, disabling psoriasis that is not adequately responsive to other forms of therapy, but only when the diagnosis has been established, as by biopsy and/or after dermatologic consultation. It is important to ensure that a psoriasis "flare" is not due to an undiagnosed concomitant disease affecting immune responses.

1.3 Limitation of Use

Rasuvo is not indicated for the treatment of neoplastic diseases.

2 DOSAGE AND ADMINISTRATION

2.1 Important Dosing Information

Rasuvo is a single-dose manually-triggered auto-injector for once-weekly subcutaneous use only [see Warnings and Precautions (5.5)]. Administer Rasuvo in the abdomen or the thigh. Rasuvo is only available in doses between 7.5 to 30 mg in 2.5 mg increments. Use another formulation of methotrexate for alternative dosing in patients who require oral, intramuscular, intravenous, intra-arterial, or intrathecal dosing, doses less than 7.5 mg per week, doses more than 30 mg per week, high-dose regimens, or dose adjustments of less than 2.5 mg increments.

2.2 Rheumatoid Arthritis including Polyarticular Juvenile Idiopathic Arthritis

Recommended starting dose of methotrexate:

Adult RA: 7.5 mg as a single oral or subcutaneous dose once weekly.

pJIA: 10 mg/m^2 once weekly.

For patients switching from oral methotrexate to Rasuvo, consider any differences in bioavailability between oral and subcutaneously administered methotrexate [see Clinical Pharmacology (12.3)].

Dosages may be adjusted gradually to achieve an optimal response. Limited experience shows a significant increase in the incidence and severity of serious toxic reactions, especially bone marrow suppression, at doses greater than 20 mg/wk in adults. Although there is experience with doses up to 30 mg/m^2/wk in children, there are too few published data to assess how doses over 20 mg/m^2/wk might affect the risk of serious toxicity in children. Experience does suggest, however, that children receiving 20 to 30 mg/m^2/wk (0.65 to 1.0 mg/kg/wk) may have better absorption and fewer gastrointestinal side effects if methotrexate is administered either intramuscularly or subcutaneously.

Therapeutic response usually begins within 3 to 6 weeks and the patient may continue to improve for another 12 weeks or more.

The optimal duration of therapy is unknown. Limited data available from long-term studies in adults indicate that the initial clinical improvement is maintained for at least two years with continued therapy. When methotrexate is discontinued, the arthritis usually worsens within 3 to 6 weeks.

The patient should be fully informed of the risks involved and should be under constant supervision of the physician. Assessment of hematologic, hepatic, renal, and pulmonary function should be made by history, physical examination, and laboratory tests before beginning, periodically during, and before reinstituting Rasuvo therapy [see Warnings and Precautions (5.4)]. Females of childbearing potential should not be started on Rasuvo until pregnancy is excluded [see Contraindications (4) and Warnings and Precautions (5.2)].

All schedules should be continually tailored to the individual patient. An initial test dose may be given prior to the regular dosing schedule to detect any extreme sensitivity to adverse effects.

Maximal myelosuppression usually occurs in seven to ten days.

2.3 Psoriasis

Recommended starting dose of methotrexate:

Psoriasis: 10-25 mg as a single oral, intramuscular, subcutaneous, or intravenous dose once weekly.

For patients switching from oral methotrexate to Rasuvo, consider any differences in bioavailability between oral and subcutaneously administered methotrexate [see Clinical Pharmacology (12.3)].

Dosage may be gradually adjusted to achieve optimal clinical response; 30 mg/week should not ordinarily be exceeded. Once optimal clinical response has been achieved, the dosage should be reduced to the lowest possible amount of drug and to the longest possible rest period. The use of Rasuvo may permit the return to conventional topical therapy, which should be encouraged.

2.4 Administration and Handling

Rasuvo is a manually-triggered auto-injector intended for subcutaneous use under the guidance and supervision of a physician.

Patients may self-inject with Rasuvo if a physician determines that it is appropriate, if they have received proper training in how to prepare and administer the correct dose, and if they receive medical follow-up, as necessary.

Rasuvo is injected once weekly. The patient must be explicitly informed about the once weekly dosing schedule. It is advisable to determine an appropriate fixed day of the week for the injection.

Visually inspect Rasuvo for particulate matter and discoloration prior to administration. Do not use Rasuvo if the seal is broken.

Handle and dispose of Rasuvo consistent with recommendations for handling and disposal of cytotoxic drugs^1.

2.5 Pregnancy testing

Verify the pregnancy status of females of reproductive potential prior to initiating treatment with Rasuvo [see Use in Specific Populations (8.1, 8.3)]

3 DOSAGE FORMS AND STRENGTHS

Rasuvo is an injection containing methotrexate at a concentration of 50 mg/ml available as a manually-triggered auto-injector that administers a single dose of methotrexate solution in the following dosage strengths:

- 7.5 mg
- 10 mg
- 12.5 mg
- 15 mg
- 17.5 mg
- 20 mg
- 22.5 mg
- 25 mg
- 27.5 mg
- 30 mg

4 CONTRAINDICATIONS

Rasuvo is contraindicated in the following:

• Pregnancy
Rasuvo can cause embryo-fetal toxicity and fetal death when administered during pregnancy. [see Warnings and Precautions (5.2) and Use in Specific Populations (8.1)].

• Alcoholism or Liver Disease
Patients with alcoholism, alcoholic liver disease or other chronic liver disease [see Warnings and Precautions (5.1)].

• Immunodeficiency Syndromes
Patients who have overt or laboratory evidence of immunodeficiency syndromes [see Warnings and Precautions (5.1)].

• Preexisting Blood Dyscrasias
Patients who have preexisting blood dyscrasias, such as bone marrow hypoplasia, leukopenia, thrombocytopenia, or significant anemia [see Warnings and Precautions (5.1)].

• Hypersensitivity
Patients with a known hypersensitivity to methotrexate. Severe hypersensitivity reactions have been observed with methotrexate use [see Warnings and Precautions (5.1) and Adverse Reactions (6.1 and 6.2)].

5 WARNINGS AND PRECAUTIONS

5.1 Organ System Toxicity

Rasuvo should be used only by physicians whose knowledge and experience include the use of antimetabolite therapy. Because of the possibility of serious toxic reactions (which can be fatal), Rasuvo should be used only in patients with psoriasis or rheumatoid arthritis with severe, recalcitrant, disabling disease which is not adequately responsive to other forms of therapy.

Deaths have been reported with the use of methotrexate in the treatment of malignancy, psoriasis, and rheumatoid arthritis. Patients should be closely monitored for bone marrow, liver, lung and kidney toxicities.

Rasuvo has the potential for serious toxicity. Toxic effects may be related in frequency and severity to dose or frequency of administration but have been seen at all doses. Because they can occur at any time during therapy, it is necessary to follow patients on Rasuvo closely. Most adverse reactions are reversible if detected early. When such reactions do occur, the drug should be reduced in dosage or discontinued and appropriate corrective measures should be taken. If necessary, this could include the use of leucovorin calcium and/or acute, intermittent hemodialysis with a high-flux dialyzer [see Overdosage (10)]. If Rasuvo therapy is reinstituted, it should be carried out with caution, with adequate consideration of further need for the drug and increased alertness as to possible recurrence of toxicity. The clinical pharmacology of methotrexate has not been well studied in older individuals. Due to diminished hepatic and renal function as well as decreased folate stores in this population, relatively low doses should be considered, and these patients should be closely monitored for early signs of toxicity [see Use in Specific Populations (8.5)].

Gastrointestinal:

Diarrhea and ulcerative stomatitis require interruption of therapy: otherwise, hemorrhagic enteritis and death from intestinal perforation may occur.

If vomiting, diarrhea, or stomatitis occur, which may result in dehydration, Rasuvo should be discontinued until recovery occurs. Rasuvo should be used with extreme caution in the presence of peptic ulcer disease or ulcerative colitis.

Unexpectedly severe (sometimes fatal) gastrointestinal toxicity has been reported with concomitant administration of methotrexate (usually in high dosage) along with some nonsteroidal anti-inflammatory drugs (NSAIDs) [see Drug Interactions (7.1)].

Hematologic:

Rasuvo can suppress hematopoiesis and cause anemia, aplastic anemia, pancytopenia, leukopenia, neutropenia, and/or thrombocytopenia. In patients with preexisting hematopoietic impairment, Rasuvo should be used with caution, if at all. In controlled clinical trials conducted with another formulation of methotrexate in rheumatoid arthritis (n=128), leukopenia (WBC <3000/mm3) was seen in 2 patients, thrombocytopenia (platelets <100,000/mm^3) in 6 patients, and pancytopenia in 2 patients.

Rasuvo should be stopped immediately if there is a significant drop in blood counts. Patients with profound granulocytopenia and fever should be evaluated immediately and usually require parenteral broad-spectrum antibiotic therapy.

Unexpectedly severe (sometimes fatal) bone marrow suppression and aplastic anemia have been reported with concomitant administration of methotrexate (usually in high dosage) along with some nonsteroidal anti- inflammatory drugs (NSAIDs) [see Drug Interactions (7.1)].

Hepatic:

Rasuvo has the potential for acute (elevated transaminases) and chronic (fibrosis and cirrhosis) hepatotoxicity. Chronic toxicity is potentially fatal; it generally has occurred after prolonged use (generally two years or more) and after a total dose of at least 1.5 grams. In studies in psoriatic patients, hepatotoxicity appeared to be a function of total cumulative dose and appeared to be enhanced by alcoholism, obesity, diabetes and advanced age. An accurate incidence rate has not been determined; the rate of progression and reversibility of lesions is not known. Special caution is indicated in the presence of preexisting liver damage or impaired hepatic function.

In psoriasis, liver function tests, including serum albumin, should be performed periodically prior to dosing but are often normal in the face of developing fibrosis or cirrhosis. These lesions may be detectable only by biopsy. The usual recommendation is to obtain a liver biopsy at 1) pretherapy or shortly after initiation of therapy (2 to 4 months), 2) a total cumulative dose of 1.5 grams, and 3) after each additional 1.0 to 1.5 grams. Moderate fibrosis or any cirrhosis normally leads to discontinuation of the drug; mild fibrosis normally suggests a repeat biopsy in 6 months.

Milder histologic findings such as fatty change and low grade portal inflammation are relatively common pretherapy. Although these mild changes are usually not a reason to avoid or discontinue Rasuvo therapy, the drug should be used with caution.

In rheumatoid arthritis, age at first use of methotrexate and duration of therapy have been reported as risk factors for hepatotoxicity; other risk factors, similar to those observed in psoriasis, may be present in rheumatoid arthritis but have not been confirmed to date. Persistent abnormalities in liver function tests may precede appearance of fibrosis or cirrhosis in this population. There is a combined reported experience in 217 rheumatoid arthritis patients with liver biopsies both before and during treatment (after a cumulative dose of at least 1.5 g) and in 714 patients with a biopsy only during treatment. There are 64 (7%) cases of fibrosis and 1 (0.1%) case of cirrhosis. Of the 64 cases of fibrosis, 60 were deemed mild. The reticulin stain is more sensitive for early fibrosis and its use may increase these figures. It is unknown whether even longer use will increase these risks.

Liver function tests should be performed at baseline and at 4 to 8 week intervals in patients receiving Rasuvo for rheumatoid arthritis. Pretreatment liver biopsy should be performed for patients with a history of excessive alcohol consumption, persistently abnormal baseline liver function test values or chronic hepatitis B or C infection. During therapy, liver biopsy should be performed if there are persistent liver function test abnormalities or there is a decrease in serum albumin below the normal range (in the setting of well controlled rheumatoid arthritis).

If the results of a liver biopsy show mild changes (Roenigk, grades I, II, IIIa), Rasuvo may be continued and the patient monitored as per recommendations listed above. Rasuvo should be discontinued in any patient who displays persistently abnormal liver function tests and refuses liver biopsy or in any patient whose liver biopsy shows moderate to severe changes (Roenigk grade IIIb or IV).

Infection or Immunologic States:

Rasuvo should be used with extreme caution in the presence of active infection, and is contraindicated in patients with overt or laboratory evidence of immunodeficiency syndromes.

Immunization may be ineffective when given during Rasuvo therapy. Immunization with live virus vaccines is generally not recommended. There have been reports of disseminated vaccinia infections after smallpox immunizations in patients receiving methotrexate therapy. Hypogammaglobulinemia has been reported rarely.

Potentially fatal opportunistic infections, especially Pneumocystis jiroveci pneumonia, may occur with Rasuvo therapy. When a patient presents with pulmonary symptoms, the possibility of Pneumocystis jiroveci pneumonia should be considered.

Neurologic:

There have been reports of leukoencephalopathy following intravenous administration of methotrexate to patients who have had craniospinal irradiation. Serious neurotoxicity, frequently manifested as generalized or focal seizures, has been reported with unexpectedly increased frequency among pediatric patients with acute lymphoblastic leukemia who were treated with intermediate-dose intravenous methotrexate (1 gm/m^2). Symptomatic patients were commonly noted to have leukoencephalopathy and/or microangiopathic calcifications on diagnostic imaging studies. Chronic leukoencephalopathy has also been reported in patients who received repeated doses of high-dose methotrexate with leucovorin rescue even without cranial irradiation.

Discontinuation of methotrexate does not always result in complete recovery. A transient acute neurologic syndrome has been observed in patients treated with high dose regimens. Manifestations of this stroke-like encephalopathy may include confusion, hemiparesis, transient blindness, seizures and coma. The exact cause is unknown. After the intrathecal use of methotrexate, the central nervous system toxicity which may occur can be classified as follows: acute chemical arachnoiditis manifested by such symptoms as headache, back pain, nuchal rigidity, and fever; sub-acute myelopathy characterized by paraparesis/paraplegia associated with involvement with one or more spinal nerve roots; chronic leukoencephalopathy manifested by confusion, irritability, somnolence, ataxia, dementia, seizures and coma. This condition can be progressive and even fatal.

Pulmonary:

Methotrexate-induced lung disease, including acute or chronic interstitial pneumonitis, is a potentially dangerous lesion, which may occur acutely at any time during therapy and has been reported at low doses. It is not always fully reversible and fatalities have been reported.

Pulmonary symptoms (especially a dry nonproductive cough) or a non-specific pneumonitis occurring during Rasuvo therapy may be indicative of a potentially dangerous lesion and require interruption of treatment and careful investigation. Although clinically variable, the typical patient with methotrexate induced lung disease presents with fever, cough, dyspnea, hypoxemia, and an infiltrate on chest X-ray; infection (including pneumonia) needs to be excluded. This lesion can occur at all dosages.

Renal:

Rasuvo may cause renal damage that may lead to acute renal failure. High doses of methotrexate used in the treatment of osteosarcoma may cause renal damage leading to acute renal failure. Nephrotoxicity is due primarily to the precipitation of methotrexate and 7-hydroxymethotrexate in the renal tubules. Close attention to renal function including adequate hydration, urine alkalinization and measurement of serum methotrexate and creatinine levels are essential for safe administration.

Skin:

Severe, occasionally fatal, dermatologic reactions, including toxic epidermal necrolysis, Stevens- Johnson syndrome, exfoliative dermatitis, skin necrosis, and erythema multiforme, have been reported in children and adults, within days of oral, intramuscular, intravenous, or intrathecal methotrexate administration. Reactions were noted after single or multiple low, intermediate, or high doses of methotrexate in patients with neoplastic and non-neoplastic diseases.

Lesions of psoriasis may be aggravated by concomitant exposure to ultraviolet radiation.

Radiation dermatitis and sunburn may be "recalled" by the use of methotrexate.

Other precautions:

Rasuvo should be used with extreme caution in the presence of debility.

Methotrexate exits slowly from third space compartments (e.g., pleural effusions or ascites). This results in a prolonged terminal plasma half-life and unexpected toxicity. In patients with significant third space accumulations, it is advisable to evacuate the fluid before treatment and to monitor plasma methotrexate levels.

5.2 Embryo-Fetal Toxicity

Based on published reports and methotrexate's mechanism of action, methotrexate can cause embryo-fetal toxicity, including fetal death when administered to a pregnant woman. In pregnant women Rasuvo is contraindicated. Verify the pregnancy status of females of reproductive potential prior to initiating Rasuvo. Advise females of reproductive potential to use effective contraception during treatment with Rasuvo and for 6 months after the final dose. Advise males of reproductive potential to use effective contraception during Rasuvo treatment and for 3 months after the final dose [see Contraindications (4), Use in Specific Populations (8.1, 8.3), Clinical Pharmacology (12.1)].

5.3 Effects on Reproduction

Based on published reports, methotrexate can cause impairment of fertility, oligospermia, and menstrual dysfunction. It is not known if the infertility may be reversible in affected patients. Discuss the risk of effects on reproduction with female and male patients of reproductive potential [see Use in Specific Populations (8.3)].

5.4 Laboratory Tests

Patients undergoing Rasuvo therapy should be closely monitored so that toxic effects are detected promptly. Baseline assessment should include a complete blood count with differential and platelet counts, hepatic enzymes, renal function tests and a chest X-ray.

During therapy, monitoring of these parameters is recommended: hematology at least monthly, renal function and liver function every 1 to 2 months [see Warnings and Precautions (5.1)].

During initial or changing doses, or during periods of increased risk of elevated methotrexate blood levels (e.g., dehydration), more frequent monitoring may also be indicated.

Liver Function Tests

Transient liver function test abnormalities are observed frequently after methotrexate administration and are usually not cause for modification of methotrexate therapy. Persistent liver function test abnormalities, and/or depression of serum albumin may be indicators of serious liver toxicity and require evaluation [see Warnings and Precautions (5.1)].

A relationship between abnormal liver function tests and fibrosis or cirrhosis of the liver has not been established for patients with psoriasis. Persistent abnormalities in liver function tests may precede appearance of fibrosis or cirrhosis in the rheumatoid arthritis population.

Pulmonary Function Tests

Pulmonary function tests may be useful if methotrexate-induced lung disease is suspected, especially if baseline measurements are available [see Warnings and Precautions (5.1)].

5.5 Risks from Improper Dosing

Both the physician and pharmacist should emphasize to the patient that Rasuvo is administered once weekly and that mistaken daily use has led to fatal toxicity [see Dosage and Administration (2)].

5.6 Patients with Impaired Renal Function, Ascites, or Pleural Effusions

Methotrexate elimination is reduced in patients with impaired renal function, ascites, or pleural effusions. Such patients require especially careful monitoring for toxicity and require dose reduction or, in some cases, discontinuation of Rasuvo administration.

5.7 Dizziness and Fatigue

Adverse reactions, such as dizziness and fatigue, may affect the ability to drive or operate machinery.

5.8 Malignant Lymphomas

Non-Hodgkin's lymphoma and other tumors have been reported in patients receiving low-dose oral methotrexate. However, there have been instances of malignant lymphoma arising during treatment with low-dose oral methotrexate, which have regressed completely following withdrawal of methotrexate, without requiring active anti-lymphoma treatment. Discontinue Rasuvo first and, if the lymphoma does not regress, appropriate treatment should be instituted.

5.9 Tumor Lysis Syndrome

Like other cytotoxic drugs, methotrexate may induce "tumor lysis syndrome" in patients with rapidly growing tumors.

5.10 Concomitant Radiation Therapy

Methotrexate given concomitantly with radiotherapy may increase the risk of soft tissue necrosis and osteonecrosis.

6 ADVERSE REACTIONS

The following adverse reactions are discussed in more detail in other sections of the labeling.

- Organ System Toxicity [see Warnings and Precautions (5.1)]
- Embryo-Fetal Toxicity [see Warnings and Precautions (5.2)]
- Effects on Reproduction [see Warnings and Precautions (5.3)]
- Malignant Lymphomas [see Warnings and Precautions (5.8)]

The most frequently reported adverse reactions include ulcerative stomatitis, leukopenia, nausea, and abdominal distress. Other frequently reported adverse reactions are malaise, undue fatigue, chills and fever, dizziness and decreased resistance to infection.

6.1 Clinical Trials Experience

This section provides a summary of adverse reactions reported in subjects in clinical studies conducted with Rasuvo as well as with methotrexate injection and oral methotrexate.

Because clinical trials are conducted under widely varying conditions, adverse reaction rates observed in the clinical trials of a drug cannot be directly compared to rates in the clinical trials of another drug, and may not reflect the rates observed in practice.

Rheumatoid Arthritis

The approximate incidences of methotrexate-attributed (i.e. placebo rate subtracted) adverse reactions in 12 to 18 week double-blind studies of patients (n=128) with rheumatoid arthritis treated with low-dose oral (7.5 to 15 mg/week) pulse methotrexate, are listed below. Virtually all of these patients were on concomitant nonsteroidal anti-inflammatory drugs and some were also taking low dosages of corticosteroids. Hepatic histology was not examined in these short-term studies.

Incidence greater than 10%: Elevated liver function tests 15%, nausea/vomiting 10%.

Incidence 3% to 10%: Stomatitis, thrombocytopenia (platelet count less than 100,000/mm3).

Incidence 1% to 3%: Rash/pruritis/dermatitis, diarrhea, alopecia, leukopenia (WBC less than 3000/mm3), pancytopenia, dizziness.

Two other controlled trials of patients (n=680) with Rheumatoid Arthritis on 7.5 mg to 15 mg/wk oral doses showed an incidence of interstitial pneumonitis of 1%.

Other less common reactions included decreased hematocrit, headache, upper respiratory infection, anorexia, arthralgias, chest pain, coughing, dysuria, eye discomfort, epistaxis, fever, infection, sweating, tinnitus, and vaginal discharge.

Polyarticular Juvenile Idiopathic Arthritis

The approximate incidences of adverse reactions reported in pediatric patients with pJIA treated with oral, weekly doses of methotrexate (5 to 20 mg/m^2/wk or 0.1 to 0.65 mg/kg/wk) were as follows (virtually all patients were receiving concomitant nonsteroidal anti-inflammatory drugs, and some also were taking low doses of corticosteroids): elevated liver function tests, 14%; gastrointestinal reactions (e.g., nausea, vomiting, diarrhea), 11%; stomatitis, 2%; leukopenia, 2%; headache, 1.2%; alopecia, 0.5%; dizziness, 0.2%; and rash, 0.2%. Although there is experience with dosing up to 30 mg/m^2/wk in pJIA, the published data for doses above 20 mg/m^2/wk are too limited to provide reliable estimates of adverse reaction rates.

Psoriasis

There are two literature reports (Roenigk, 1969, and Nyfors, 1978) describing large series (n=204, 248) of psoriasis patients treated with methotrexate. Dosages ranged up to 25 mg per week and treatment was administered for up to four years. With the exception of alopecia, photosensitivity, and "burning of skin lesions" (each 3% to 10%), the adverse reaction rates in these reports were very similar to those in the rheumatoid arthritis studies. Rarely, painful plaque erosions may appear (Pearce, HP and Wilson, BB: Am Acad Dermatol 35: 835-838, 1996).

6.2 Other Adverse Reactions

Other adverse reactions that have been reported with methotrexate in oncology, RA, pJIA, and psoriasis patients are listed below by organ system.

Alimentary System: gingivitis, pharyngitis, stomatitis, anorexia, nausea, vomiting, diarrhea, hematemesis, melena, gastrointestinal ulceration and bleeding, enteritis, pancreatitis.

Blood and Lymphatic System Disorders: suppressed hematopoiesis, anemia, aplastic anemia, pancytopenia, leukopenia, neutropenia, thrombocytopenia, agranulocytosis, eosinophilia, lymphadenopathy and lymphoproliferative disorders (including reversible). Hypogammaglobulinemia has been reported rarely.

Cardiovascular: pericarditis, pericardial effusion, hypotension, and thromboembolic events (including arterial thrombosis, cerebral thrombosis, deep vein thrombosis, retinal vein thrombosis, thrombophlebitis, and pulmonary embolus).

Central Nervous System: headaches, drowsiness, blurred vision, transient blindness, speech impairment including dysarthria and aphasia, hemiparesis, paresis and convulsions have also occurred following administration of methotrexate. Following low doses, there have been occasional reports of transient subtle cognitive dysfunction, mood alteration or unusual cranial sensations, leukoencephalopathy, or encephalopathy.

Hepatobiliary Disorders: hepatotoxicity, acute hepatitis, chronic fibrosis and cirrhosis, hepatic failure, decrease in serum albumin, liver enzyme elevations.

Infection: There have been case reports of sometimes fatal opportunistic infections in patients receiving methotrexate therapy for neoplastic and non-neoplastic diseases. Pneumocystis jiroveci pneumonia was the most common opportunistic infection. There have also been reports of infections, pneumonia, Cytomegalovirus infection, including cytomegaloviral pneumonia, sepsis, fatal sepsis, nocardiosis, histoplasmosis, cryptococcosis, Herpes zoster, Herpes simplex hepatitis, and disseminated Herpes simplex.

Musculoskeletal System: stress fracture.

Ophthalmic: conjunctivitis, serious visual changes of unknown etiology.

Pulmonary System: respiratory fibrosis, respiratory failure, alveolitis, interstitial pneumonitis deaths have been reported, and chronic interstitial obstructive pulmonary disease has occasionally occurred.

Skin: erythematous rashes, pruritus, urticaria, photosensitivity, pigmentary changes, alopecia, ecchymosis, telangiectasia, acne, furunculosis, erythema multiforme, toxic epidermal necrolysis, Stevens-Johnson syndrome, skin necrosis, skin ulceration and exfoliative dermatitis.

Urogenital System: severe nephropathy or renal failure, azotemia, cystitis, hematuria, proteinuria; defective oogenesis or spermatogenesis, transient oligospermia, menstrual dysfunction, vaginal discharge, and gynecomastia; infertility, abortion, fetal death, fetal defects.

Other rarer reactions related to or attributed to the use of methotrexate such as nodulosis, vasculitis, arthralgia/myalgia, loss of libido/impotence, diabetes, osteoporosis, sudden death, lymphoma, including reversible lymphomas, tumor lysis syndrome, soft tissue necrosis and osteonecrosis. Anaphylactoid reactions have been reported.

7 DRUG INTERACTIONS

7.1 Aspirin, Nonsteroidal Anti-Inflammatory Drugs, and Steroids

Nonsteroidal anti-inflammatory drugs (NSAIDs) should not be administered prior to or concomitantly with the high doses of methotrexate, such as used in the treatment of osteosarcoma. Concomitant administration of some NSAIDs with high dose methotrexate therapy has been reported to elevate and prolong serum methotrexate levels, resulting in deaths from severe hematologic and gastrointestinal toxicity [see Warnings and Precautions (5.1)].

Caution should be used when NSAIDs and salicylates are administered concomitantly with lower doses of methotrexate, including Rasuvo. These drugs have been reported to reduce the tubular secretion of methotrexate in an animal model and may enhance its toxicity.

Despite the potential interactions, studies of methotrexate in patients with rheumatoid arthritis have usually included concurrent use of constant dosage regimens of NSAIDs, without apparent problems. It should be appreciated, however, that the doses used in rheumatoid arthritis (7.5 to 15 mg/week) are somewhat lower than those used in psoriasis and that larger doses could lead to unexpected toxicity. Aspirin, NSAIDs, and/or low dose steroids may be continued, although the possibility of increased toxicity with concomitant use of NSAIDs including salicylates has not been fully explored. Steroids may be reduced gradually in patients who respond to methotrexate.

7.2 Proton Pump Inhibitors (PPIs) and H2 Blockers

Use caution if high-dose methotrexate is administered to patients receiving proton pump inhibitor (PPI) therapy. Case reports and published population pharmacokinetic studies suggest that concomitant use of some PPIs, such as omeprazole, esomeprazole, and pantoprazole, with methotrexate (primarily at high dose), may elevate and prolong serum levels of methotrexate and/or its metabolite hydroxymethotrexate, possibly leading to methotrexate toxicities. In two of these cases, delayed methotrexate elimination was observed when high-dose methotrexate was co-administered with PPIs, but was not observed when methotrexate was co-administered with ranitidine. However, no formal drug interaction studies of methotrexate with ranitidine have been conducted.

7.3 Oral Antibiotics

Oral antibiotics such as tetracycline, chloramphenicol, and nonabsorbable broad spectrum antibiotics, may decrease intestinal absorption of methotrexate or interfere with the enterohepatic circulation by inhibiting bowel flora and suppressing metabolism of the drug by bacteria.

Penicillins may reduce the renal clearance of methotrexate; increased serum concentrations of methotrexate with concomitant hematologic and gastrointestinal toxicity have been observed with high and low dose methotrexate. Use of Rasuvo with penicillins should be carefully monitored.

Trimethoprim/sulfamethoxazole has been reported rarely to increase bone marrow suppression in patients receiving methotrexate, probably by decreased tubular secretion and/or an additive antifolate effect.

7.4 Hepatotoxins

The potential for increased hepatotoxicity when methotrexate is administered with other hepatotoxic agents has not been evaluated. However, hepatotoxicity has been reported in such cases. Therefore, patients receiving concomitant therapy with Rasuvo and other potential hepatotoxins (e.g., azathioprine, retinoids, and sulfasalazine) should be closely monitored for possible increased risk of hepatotoxicity.

7.5 Theophylline

Methotrexate may decrease the clearance of theophylline; theophylline levels should be monitored when used concurrently with Rasuvo.

7.6 Folic Acid and Antifolates

Vitamin preparations containing folic acid or its derivatives may decrease responses to systemically administered methotrexate. Preliminary animal and human studies have shown that small quantities of intravenously administered leucovorin enter the CSF primarily as 5-methyltetrahydrofolate and, in humans, remain 1 to 3 orders of magnitude lower than the usual methotrexate concentrations following intrathecal administration. However, high doses of leucovorin may reduce the efficacy of intrathecally administered methotrexate. Folate deficiency states may increase methotrexate toxicity.

Trimethoprim/sulfamethoxazole has been reported rarely to increase bone marrow suppression in patients receiving methotrexate, probably by decreased tubular secretion and/or an additive antifolate effect.

7.7 Mercaptopurine

Methotrexate increases the plasma levels of mercaptopurine. The combination of Rasuvo and mercaptopurine may therefore require dose adjustment.

7.8 Nitrous oxide

The use of nitrous oxide anesthesia potentiates the effect of methotrexate on folate dependent metabolic pathways, resulting in the potential for increased toxicity. Avoid the simultaneous use of nitrous oxide and methotrexate.

7.9 Other Drugs

Methotrexate is partially bound to serum albumin, and toxicity may be increased because of displacement by certain drugs, such as salicylates, phenylbutazone, phenytoin, and sulfonamides.

Renal tubular transport is also diminished by probenecid; use of Rasuvo with this drug should be carefully monitored.

Combined use of methotrexate with gold, penicillamine, hydroxychloroquine, sulfasalazine, or cytotoxic agents, has not been studied and may increase the incidence of adverse effects.

8 USE IN SPECIFIC POPULATIONS

8.1 Pregnancy

Risk Summary

Based on published reports, and methotrexate's mechanism of action, methotrexate can cause embryo-fetal toxicity and fetal death when administered to a pregnant woman [see Data and Clinical Pharmacology (12.1)]. In pregnant women with psoriasis or rheumatoid arthritis, Rasuvo is contraindicated [see Contraindications (4)]. There are no animal data that meet current standards for nonclinical developmental toxicity studies.

The estimated background risk of major birth defects and miscarriage for the indicated populations are unknown. All pregnancies have a background risk of birth defect, loss, or other adverse outcomes. In the U.S. general population, the estimated background risk of major birth defects and miscarriage in clinically recognized pregnancies is 2 – 4 % and 15 – 20 %, respectively.

Data

Human Data

Published data from cases, literature reviews, and observational studies report that methotrexate exposure during pregnancy is associated with an increased risk of embryo-fetal toxicity and fetal death. Methotrexate exposure during the first trimester of pregnancy is associated with an increased incidence of spontaneous abortions and multiple adverse developmental outcomes, including skull anomalies, facial dysmorphism, central nervous system abnormalities, limb abnormalities, and sometimes cardiac anomalies and intellectual impairment. Adverse outcomes associated with exposure during second and third trimesters of pregnancy include intrauterine growth restriction and functional abnormalities. Because methotrexate is widely distributed and persists in the body for a prolonged period, there is a potential risk to the fetus from preconception methotrexate exposure.

A prospective multicenter study evaluated pregnancy outcomes in women taking methotrexate less than or equal to 30 mg/week after conception. The rate of miscarriage in pregnant women exposed to methotrexate was 42.5% (95% confidence interval [95% CI] 29.2-58.7), which was higher than in unexposed patients with autoimmune disease (22.5%, 95% CI 16.8-29.7) and unexposed patients with non-autoimmune disease (17.3%, 95% CI 13-22.8). Of the live births, the rate of major birth defects in pregnant women exposed to methotrexate after conception was higher than in unexposed patients with autoimmune disease (adjusted odds ratio (OR) 1.8 [95% CI 0.6-5.7]) and unexposed patients with non-autoimmune disease (adjusted OR 3.1 [95% CI 1.03-9.5]) (2.9%).Major birth defects associated with pregnancies exposed to methotrexate after conception were not always consistent with methotrexate-associated adverse developmental outcomes.

8.2 Lactation

Risk Summary

Limited published literature report the presence of methotrexate in human breast milk in low amounts following oral methotrexate administration, with the highest breast milk to plasma concentration ratio reported to be 0.08:1. No information is available on the effects of methotrexate on a breastfed infant or on milk production. Because of the potential for serious adverse reactions from methotrexate in breastfed infants, including myelosuppression advise women not to breastfeed during treatment with Rasuvo and for one week after the final dose.

8.3 Females and Males of Reproductive Potential

Pregnancy Testing

Verify the pregnancy status of females of reproductive potential prior to initiating Rasuvo.

Contraception

Females

Rasuvo can cause fetal harm when administered to a pregnant woman [see Use in Specific Populations (8.1)]. Advise females of reproductive potential to use effective contraception during and for 6 months after the final dose of Rasuvo.

Males

Methotrexate can cause chromosomal damage to sperm cells. Advise males with female partners of reproductive potential to use effective contraception during and for at least 3 months after the final dose of Rasuvo.

Infertility

Females

Based on the published reports of female infertility after treatment with methotrexate, advise females of reproductive potential that Rasuvo can cause impairment of fertility and menstrual dysfunction during and after cessation of therapy. It is not known if the infertility may be reversed in all affected females.

Males

Based on published reports of male infertility after treatment with methotrexate, advise males of reproductive potential that Rasuvo can cause infertility or oligospermia during and after cessation of therapy. It is not known if the infertility may be reversed in all affected males.

8.4 Pediatric Use

The safety and effectiveness of methotrexate, including Rasuvo, have not been established in pediatric patients with psoriasis.

The safety and effectiveness of Rasuvo have not been established in pediatric patients with neoplastic diseases.

The safety and effectiveness of methotrexate have been established in pediatric patients with polyarticular juvenile idiopathic arthritis [see Clinical Studies (14.2)].

Published clinical studies evaluating the use of methotrexate in children and adolescents (i.e., patients 2 to 16 years of age) with pJIA demonstrated safety comparable to that observed in adults with rheumatoid arthritis [see Adverse Reactions (6.1)].

Rasuvo does not contain a preservative. However, methotrexate injectable formulations containing the preservative benzyl alcohol are not recommended for use in neonates. There have been reports of fatal 'gasping syndrome' in neonates (children less than one month of age) following the administrations of intravenous solutions containing the preservative benzyl alcohol. Symptoms include a striking onset of gasping respiration, hypotension, bradycardia, and cardiovascular collapse.

Serious neurotoxicity, frequently manifested as generalized or focal seizures, has been reported with unexpectedly increased frequency among pediatric patients with acute lymphoblastic leukemia who were treated with intermediate-dose intravenous methotrexate (1 gm/m^2) [see Warnings and Precautions (5.1)].

8.5 Geriatric Use

Clinical studies of methotrexate did not include sufficient numbers of subjects age 65 and over to determine whether they respond differently from younger subjects. In general, dose selection for an elderly patient should be cautious reflecting the greater frequency of decreased hepatic and renal function, decreased folate stores, concomitant disease or other drug therapy (i.e., that interfere with renal function, methotrexate or folate metabolism) in this population [see Warnings and Precautions (5.1), Drug Interactions (7.7) and Use in Specific Populations (8.6)]. Since decline in renal function may be associated with increases in adverse reactions and serum creatinine measurements may over estimate renal function in the elderly, more accurate methods (i.e., creatinine clearance) should be considered. Serum methotrexate levels may also be helpful. Elderly patients should be closely monitored for early signs of hepatic, bone marrow and renal toxicity. In chronic use situations, certain toxicities may be reduced by folate supplementation.

Post-marketing experience suggests that the occurrence of bone marrow suppression, thrombocytopenia, and pneumonitis may increase with age [see Warnings and Precautions (5.1)].

8.6 Renal Impairment

Methotrexate elimination is reduced in patients with impaired renal function. Such patients require especially careful monitoring for toxicity and require dose reduction or, in some cases, discontinuation of Rasuvo administration.

8.7 Hepatic Impairment

The effect of hepatic impairment on methotrexate pharmacokinetics has not been studied. Rasuvo is contraindicated in patients with alcoholic liver disease or other chronic liver disease. Patients with obesity, diabetes, hepatic fibrosis or steatohepatitis are at increased risk for hepatic injury and fibrosis secondary to methotrexate, and should be monitored closely [see Warnings and Precautions (5.1)].

10 OVERDOSAGE

Leucovorin is indicated to diminish the toxicity and counteract the effect of inadvertently administered overdosages of methotrexate. Leucovorin administration should begin as promptly as possible. As the time interval between methotrexate administration and leucovorin initiation increases, the effectiveness of leucovorin in counteracting toxicity decreases. Monitoring of the serum methotrexate concentration is essential in determining the optimal dose and duration of treatment with leucovorin.

In cases of massive overdosage, hydration and urinary alkalinization may be necessary to prevent the precipitation of methotrexate and/or its metabolites in the renal tubules. Generally speaking, neither hemodialysis nor peritoneal dialysis has been shown to improve methotrexate elimination. However, effective clearance of methotrexate has been reported with acute, intermittent hemodialysis using a high-flux dialyzer (Wall, SM et al: Am J Kidney Dis 28 (6): 846-854, 1996).

Accidental intrathecal overdosage may require intensive systemic support, high-dose systemic leucovorin, alkaline diuresis and rapid CSF drainage and ventriculolumbar perfusion.

In postmarketing experience, overdose with methotrexate has generally occurred with oral and intrathecal administration, although intravenous and intramuscular overdose have also been reported.

Reports of oral overdose often indicate accidental daily administration instead of weekly (single or divided doses). Symptoms commonly reported following oral overdose include those symptoms and signs reported at pharmacologic doses, particularly hematologic and gastrointestinal reaction. For example, leukopenia, thrombocytopenia, anemia, pancytopenia, bone marrow suppression, mucositis, stomatitis, oral ulceration, nausea, vomiting, gastrointestinal ulceration, gastrointestinal bleeding. In some cases, no symptoms were reported.

There have been reports of death following overdose. In these cases, events such as sepsis or septic shock, renal failure, and aplastic anemia were also reported.

Symptoms of intrathecal overdose are generally central nervous system (CNS) symptoms, including headache, nausea and vomiting, seizure or convulsion, and acute toxic encephalopathy. In some cases, no symptoms were reported. There have been reports of death following intrathecal overdose. In these cases, cerebellar herniation associated with increased intracranial pressure, and acute toxic encephalopathy have also been reported.

There are published case reports of intravenous and intrathecal carboxypeptidase G2 treatment to hasten clearance of methotrexate in cases of overdose.

11 DESCRIPTION

Rasuvo contains methotrexate, a folate analog metabolic inhibitor.

Chemically, methotrexate is [N-[4-[[(2,4-diamino-6-pteridinyl)methyl]methylamino]benzoyl]-Lglutamic acid. The structural formula is:

C20H22N8O5 M.W.= 454.45

Rasuvo contains methotrexate in a sterile, preservative-free, non-pyrogenic solution for a single subcutaneous injection. Rasuvo is an isotonic, clear, yellow to brown solution.

Rasuvo contains the following inactive ingredients: sodium chloride 0.4% w/v; water for injections, sodium hydroxide and, if necessary, hydrochloric acid are added to adjust the pH to approximately 8.5.

12 CLINICAL PHARMACOLOGY

12.1 Mechanism of Action

Methotrexate inhibits dihydrofolic acid reductase. Dihydrofolates must be reduced to tetrahydrofolates by this enzyme before they can be utilized as carriers of one-carbon groups in the synthesis of purine nucleotides and thymidylate. Therefore, methotrexate interferes with DNA synthesis, repair, and cellular replication. Actively proliferating tissues such as malignant cells, bone marrow, fetal cells, buccal and intestinal mucosa, and cells of the urinary bladder are in general more sensitive to this effect of methotrexate.

The mechanism of action in rheumatoid arthritis is unknown; it may affect immune function.

12.2 Pharmacodynamics

Two reports describe in vitro methotrexate inhibition of DNA precursor uptake by stimulated mononuclear cells, and another describes in animal polyarthritis partial correction by methotrexate of spleen cell hyporesponsiveness and suppressed IL 2 production. Other laboratories, however, have been unable to demonstrate similar effects. Clarification of methotrexate's effect on immune activity and its relation to rheumatoid immunopathogenesis await further studies.

In psoriasis, the rate of production of epithelial cells in the skin is greatly increased over normal skin. This differential in proliferation rates is the basis for the use of methotrexate to control the psoriatic process.

Methotrexate in high doses, followed by leucovorin rescue, is used as a part of the treatment of patients with non- metastatic osteosarcoma. The original rationale for high dose methotrexate therapy was based on the concept of selective rescue of normal tissues by leucovorin. More recent evidence suggests that high dose methotrexate may also overcome methotrexate resistance caused by impaired active transport, decreased affinity of dihydrofolic acid reductase for methotrexate, increased levels of dihydrofolic acid reductase resulting from gene amplification, or decreased polyglutamation of methotrexate. The actual mechanism of action is unknown.

12.3 Pharmacokinetics

Absorption

In adults, oral absorption appears to be dose dependent. Peak serum levels are reached within one to two hours. At doses of 30 mg/m^2 or less, methotrexate is generally well absorbed with a mean bioavailability of about 60%. The absorption of doses greater than 80 mg/m^2 is significantly less, possibly due to a saturation effect.

In a relative bioavailability study in healthy subjects, the systemic exposure of methotrexate (AUC) from Rasuvo at doses of 7.5 mg, 15 mg, 22.5 mg, and 30 mg, was higher than that of oral methotrexate administered at the same doses by 35%, 49%, 51%, and 68%, respectively. In a relative bioavailability study in psoriasis patients, the systemic exposure (AUC) of methotrexate from Rasuvo at a dose of 30 mg, was similar to that of methotrexate administered at the same dose by the intramuscular route.

In leukemic pediatric patients, oral absorption of methotrexate also appears to be dose dependent and has been reported to vary widely (23% to 95%). A twenty fold difference between highest and lowest peak levels (Cmax: 0.11 to 2.3 micromolar after a 20 mg/m^2 dose) has been reported.

Significant interindividual variability has also been noted in time to peak concentration (Tmax: 0.67 to 4 hrs after a 15 mg/m^2 dose) and fraction of dose absorbed. The absorption of doses greater than 40 mg/m2 has been reported to be significantly less than that of lower doses. Food has been shown to delay absorption and reduce peak concentration.

Methotrexate is generally completely absorbed from parenteral routes of injection. After intramuscular injection, peak serum concentrations occur in 30 to 60 minutes.

As in leukemic pediatric patients, a wide interindividual variability in the plasma concentrations of methotrexate has been reported in pediatric patients with JIA. Following oral administration of methotrexate in doses of 6.4 to 11.2 mg/m^2/week in pediatric patients with JIA, mean serum concentrations were 0.59 micromolar (range, 0.03 to 1.40) at 1 hour, 0.44 micromolar (range, 0.01 to 1.00) at 2 hours, and 0.29 micromolar (range, 0.06 to 0.58) at 3 hours.

Distribution

After intravenous administration, the initial volume of distribution is approximately 0.18 L/kg (18% of body weight) and steady-state volume of distribution is approximately 0.4 to 0.8 L/kg (40 to 80% of body weight). Methotrexate competes with reduced folates for active transport across cell membranes by means of a single carrier-mediated active transport process. At serum concentrations greater than 100 micromolar, passive diffusion becomes a major pathway by which effective intracellular concentrations can be achieved. Methotrexate in serum is approximately 50% protein bound. Laboratory studies demonstrate that it may be displaced from plasma albumin by various compounds including sulfonamides, salicylates, tetracyclines, chloramphenicol, and phenytoin.

Methotrexate does not penetrate the blood-cerebrospinal fluid barrier in therapeutic amounts when given orally or parenterally. High CSF concentrations of the drug may be attained by intrathecal administration of other parenteral forms of methotrexate.

In dogs, synovial fluid concentrations after oral dosing were higher in inflamed than uninflamed joints. Although salicylates did not interfere with this penetration, prior prednisone treatment reduced penetration into inflamed joints to the level of normal joints.

Metabolism

After absorption, methotrexate undergoes hepatic and intracellular metabolism to polyglutamated forms which can be converted back to methotrexate by hydrolase enzymes. These polyglutamates act as inhibitors of dihydrofolate reductase and thymidylate synthetase. Small amounts of methotrexate polyglutamates may remain in tissues for extended periods. The retention and prolonged drug action of these active metabolites vary among different cells, tissues and tumors. A small amount of metabolism to 7-hydroxymethotrexate may occur at doses commonly prescribed. Accumulation of this metabolite may become significant at the high doses used in osteogenic sarcoma. The aqueous solubility of 7-hydroxymethotrexate is 3 to 5 fold lower than the parent compound. Methotrexate is partially metabolized by intestinal flora after oral administration.

Half-Life

The terminal half-life reported for methotrexate is approximately three to ten hours for patients receiving treatment for psoriasis, or rheumatoid arthritis or low dose antineoplastic therapy (less than 30 mg/m^2). For patients receiving high doses of methotrexate, the terminal half-life is eight to 15 hours.

In pediatric patients receiving methotrexate for acute lymphocytic leukemia (6.3 to 30 mg/m^2), or for JIA (3.75 to 26.2 mg/m^2), the terminal half-life has been reported to range from 0.7 to 5.8 hours or 0.9 to 2.3 hours, respectively.

Excretion

Renal excretion is the primary route of elimination and is dependent upon dosage and route of administration. With IV administration, 80% to 90% of the administered dose is excreted unchanged in the urine within 24 hours. There is limited biliary excretion amounting to 10% or less of the administered dose. Enterohepatic recirculation of methotrexate has been proposed.

Renal excretion occurs by glomerular filtration and active tubular secretion. Nonlinear elimination due to saturation of renal tubular reabsorption has been observed in psoriatic patients at doses between 7.5 and 30 mg. Impaired renal function, as well as concurrent use of drugs such as weak organic acids that also undergo tubular secretion, can markedly increase methotrexate serum levels.

Excellent correlation has been reported between methotrexate clearance and endogenous creatinine clearance.

Methotrexate clearance rates vary widely and are generally decreased at higher doses. Delayed drug clearance has been identified as one of the major factors responsible for methotrexate toxicity. It has been postulated that the toxicity of methotrexate for normal tissues is more dependent upon the duration of exposure to the drug rather than the peak level achieved. When a patient has delayed drug elimination due to compromised renal function, a third space effusion, or other causes, methotrexate serum concentrations may remain elevated for prolonged periods.

When other forms of parenteral methotrexate are administered during cancer chemotherapy, the potential for toxicity from high dose regimens or delayed excretion is reduced by the administration of leucovorin calcium during the final phase of methotrexate plasma elimination.

Pharmacokinetic monitoring of methotrexate serum concentrations may help identify those patients at high risk for methotrexate toxicity and aid in proper adjustments of leucovorin dosing.

13 NONCLINICAL TOXICOLOGY

13.1 Carcinogenesis, Mutagenesis, Impairment of Fertility

Methotrexate has been evaluated in a number of animal studies for carcinogenic potential with inconclusive results. Although there is evidence that methotrexate causes chromosomal damage to animal somatic cells and human bone marrow cells, the clinical significance remains uncertain.

Data are available regarding the risks for pregnancy and for fertility in humans [see Use in Specific Populations (8.1 and 8.3)].

14 CLINICAL STUDIES

14.1 Rheumatoid Arthritis

Clinical trials in patients with rheumatoid arthritis were performed using other formulations of methotrexate.

In patients with rheumatoid arthritis, effects of methotrexate on articular swelling and tenderness can be seen as early as 3 to 6 weeks.

Most studies of methotrexate in patients with rheumatoid arthritis are relatively short term (3 to 6 months). Limited data from long-term studies indicate that an initial clinical improvement is maintained for at least two years with continued therapy.

14.2 Polyarticular Juvenile Idiopathic Arthritis

Clinical trials in patients with polyarticular juvenile idiopathic arthritis were performed using other formulations of methotrexate.

In a 6-month double-blind, placebo-controlled trial of 127 pediatric patients with pJIA (mean age, 10.1 years; age range, 2.5 to 18 years; mean duration of disease, 5.1 years) on background nonsteroidal anti-inflammatory drugs and/or prednisone, methotrexate given weekly at an oral dose of 10 mg/m^2 provided significant clinical improvement compared to placebo as measured by either the physician's global assessment, or by a patient composite (25% reduction in the articular-severity score plus improvement in parent and physician global assessments of disease activity). Over two-thirds of the patients in this trial had polyarticular-course JIA, and the numerically greatest response was seen in this subgroup treated with 10 mg/m^2/wk methotrexate.

The overwhelming majority of the remaining patients had systemic-course JIA. All patients were unresponsive to NSAIDs; approximately one-third were using low dose corticosteroids.

Weekly methotrexate at a dose of 5 mg/m2 was not significantly more effective than placebo in this trial.

15 REFERENCES

1. "Hazardous Drugs". OSHA. http://www.osha.gov/SLTC/hazardousdrugs/index.html

16 HOW SUPPLIED/STORAGE AND HANDLING

Rasuvo contains methotrexate in a preservative-free sterile solution for a single subcutaneous injection in the following configurations.

Strength | Pack Configuration [Single unit configurations are not for sale. Sample only.] | NDC
7.5 mg per 0.15 mL | 1 | 59137-505-01
 | 4 | 59137-505-04
10 mg per 0.20 mL | 1 | 59137-510-01
 | 4 | 59137-510-04
12.5 mg per 0.25 mL | 1 | 59137-515-01
 | 4 | 59137-515-04
15 mg per 0.30 mL | 1 | 59137-520-01
 | 4 | 59137-520-04
17.5 mg per 0.35 mL | 1 | 59137-525-01
 | 4 | 59137-525-04
20 mg per 0.40 mL | 1 | 59137-530-01
 | 4 | 59137-530-04
22.5 mg per 0.45 mL | 1 | 59137-535-01
 | 4 | 59137-535-04
25 mg per 0.50 mL | 1 | 59137-540-01
 | 4 | 59137-540-04
27.5 mg per 0.55 mL | 1 | 59137-545-01
 | 4 | 59137-545-04
30 mg per 0.60 mL | 1 | 59137-550-01
 | 4 | 59137-550-04

Not all pack sizes may be marketed.

STORAGE AND HANDLING

Store at controlled room temperature, 25°C (77°F); excursions permitted to 15° to 30°C (59° to 86°F). PROTECT FROM LIGHT.

Handling and Disposal

Handle and dispose of Rasuvo consistent with recommendations for handling and disposal of cytotoxic drugs.^1

17 PATIENT COUNSELING INFORMATION

See FDA-approved patient labeling (Patient Information and Instructions for Use)

Risk of Organ Toxicity

Inform patients of the risks of organ toxicity, including gastrointestinal, hematologic, hepatic, infections, neurologic, pulmonary, renal and skin as well as possible signs and symptoms for which they should contact their healthcare provider. Advise patients of the need for close follow-up, including periodic laboratory tests to monitor toxicity [see Warnings and Precautions (5.1 and 5.4)].

Importance of Proper Dosing and Administration

Both the physician and pharmacist should emphasize to the patient that the recommended dose is taken once weekly and that mistaken daily use of the recommended dose has led to fatal toxicity [see Dosage and Administration (2)].

Rasuvo is intended for use under the guidance and supervision of a physician. Patients should not self-administer until they receive training from a healthcare professional. The patient's or caregiver's ability to administer Rasuvo should be assessed.

Patients should be instructed to use administration sites on the abdomen or the thigh. Administration should not be made within 2 inches of the navel. Instruct patients not to administer Rasuvo to the arms or any other areas of the body, as delineated in the Rasuvo Instructions for Use [see Instructions for Use].

Embryo-Fetal Toxicity

- Advise females of reproductive potential that Rasuvo can cause fetal harm and is contraindicated in pregnancy. Advise women of childbearing potential that Rasuvo should not be started until pregnancy is excluded. Women should be fully counseled on the serious risk to the fetus should they become pregnant while undergoing treatment. Inform patients to contact their physician if they suspect that they are pregnant [see Boxed Warning, Contraindications (4), Warnings and Precautions (5.2), Use in Specific Populations (8.1)].
- Advise females of reproductive potential to use effective contraception during Rasuvo treatment and for 6 months after the final dose [see Use in Specific Populations (8.3)].
- Advise males of reproductive potential to use effective contraception during Rasuvo treatment and for 3 months after the final dose [see Use in Specific Populations (8.3)].

Infertility

Advise patients of reproductive potential that Rasuvo may cause impairment of fertility, oligospermia and menstrual dysfunction [see Use in Specific Populations (8.3)].

Lactation

Advise females not to breastfeed during treatment with Rasuvo and for one week after the final dose [see Use in Specific Populations (8.2)].

Ability to Drive or Operate Machinery

Inform patients that adverse reactions such as dizziness and fatigue may affect their ability to drive or operate machinery.

Proper Storage and Disposal

Advise patients to store Rasuvo at room temperature (68 to 77°F or 20 to 25°C). Inform patients and caregivers of the need for proper disposal after use, including the use of a sharps disposal container.

Manufactured for:
Medexus Pharma Inc.
29 N Wacker Drive, Suite 704
Chicago, IL 60606

Manufactured by:
Oncotec Pharma Produktion GmbH
Am Pharmapark
D-06861 Dessau-Roßlau
Germany

PRINCIPAL DISPLAY PANEL - 7.5 mg Auto-Injector Carton

NDC 59137-505-04
Rx only

7.5 mg

Rasuvo®
methotrexate
injection

Rasuvo® (methotrexate) injection

7.5 mg per 0.15 mL

This carton contains 4 pre-assembled 0.15 mL pre-filled Rasuvo auto-injectors.
FOR SUBCUTANEOUS USE ONLY
See full prescribing information for dosage and administration.
Read enclosed patient package insert carefully before using.

PRINCIPAL DISPLAY PANEL - 10 mg Auto-Injector Carton

NDC 59137-510-04
Rx only

10 mg

Rasuvo®
methotrexate
injection

Rasuvo® (methotrexate) injection

10 mg per 0.20 mL

This carton contains 4 pre-assembled 0.20 mL pre-filled Rasuvo auto-injectors.
FOR SUBCUTANEOUS USE ONLY
See full prescribing information for dosage and administration.
Read enclosed patient package insert carefully before using.

PRINCIPAL DISPLAY PANEL - 12.5 mg Auto-Injector Carton

NDC 59137-515-04
Rx only

12.5 mg

Rasuvo®
methotrexate
injection

Rasuvo® (methotrexate) injection

12.5 mg per 0.25 mL

This carton contains 4 pre-assembled 0.25 mL pre-filled Rasuvo auto-injectors.
FOR SUBCUTANEOUS USE ONLY
See full prescribing information for dosage and administration.
Read enclosed patient package insert carefully before using.

PRINCIPAL DISPLAY PANEL - 15 mg Auto-Injector Carton

NDC 59137-520-04
Rx only

15 mg

Rasuvo®
methotrexate
injection

Rasuvo® (methotrexate) injection

15 mg per 0.30 mL

This carton contains 4 pre-assembled 0.30 mL pre-filled Rasuvo auto-injectors.
FOR SUBCUTANEOUS USE ONLY
See full prescribing information for dosage and administration.
Read enclosed patient package insert carefully before using.

PRINCIPAL DISPLAY PANEL - 17.5 mg Auto-Injector Carton

NDC 59137-525-04
Rx only

17.5 mg

Rasuvo®
methotrexate
injection

Rasuvo® (methotrexate) injection

17.5 mg per 0.35 mL

This carton contains 4 pre-assembled 0.35 mL pre-filled Rasuvo auto-injectors.
FOR SUBCUTANEOUS USE ONLY
See full prescribing information for dosage and administration.
Read enclosed patient package insert carefully before using.

PRINCIPAL DISPLAY PANEL - 20 mg Auto-Injector Carton

NDC 59137-530-04
Rx only

20 mg

Rasuvo®
methotrexate
injection

Rasuvo® (methotrexate) injection

20 mg per 0.40 mL

This carton contains 4 pre-assembled 0.40 mL pre-filled Rasuvo auto-injectors.
FOR SUBCUTANEOUS USE ONLY
See full prescribing information for dosage and administration.
Read enclosed patient package insert carefully before using.

PRINCIPAL DISPLAY PANEL - 22.5 mg Auto-Injector Carton

NDC 59137-535-04
Rx only

22.5 mg

Rasuvo®
methotrexate
injection

Rasuvo® (methotrexate) injection

22.5 mg per 0.45 mL

This carton contains 4 pre-assembled 0.45 mL pre-filled Rasuvo auto-injectors.
FOR SUBCUTANEOUS USE ONLY
See full prescribing information for dosage and administration.
Read enclosed patient package insert carefully before using.

PRINCIPAL DISPLAY PANEL - 25 mg Auto-Injector Carton

NDC 59137-540-04
Rx only

25 mg

Rasuvo®
methotrexate
injection

Rasuvo® (methotrexate) injection

25 mg per 0.50 mL

This carton contains 4 pre-assembled 0.50 mL pre-filled Rasuvo auto-injectors.
FOR SUBCUTANEOUS USE ONLY
See full prescribing information for dosage and administration.
Read enclosed patient package insert carefully before using.

PRINCIPAL DISPLAY PANEL - 30 mg Auto-Injector Carton

NDC 59137-550-04
Rx only

30 mg

Rasuvo®
methotrexate
injection

Rasuvo® (methotrexate) injection

30 mg per 0.60 mL

This carton contains 4 pre-assembled 0.60 mL pre-filled Rasuvo auto-injectors.
FOR SUBCUTANEOUS USE ONLY
See full prescribing information for dosage and administration.
Read enclosed patient package insert carefully before using.